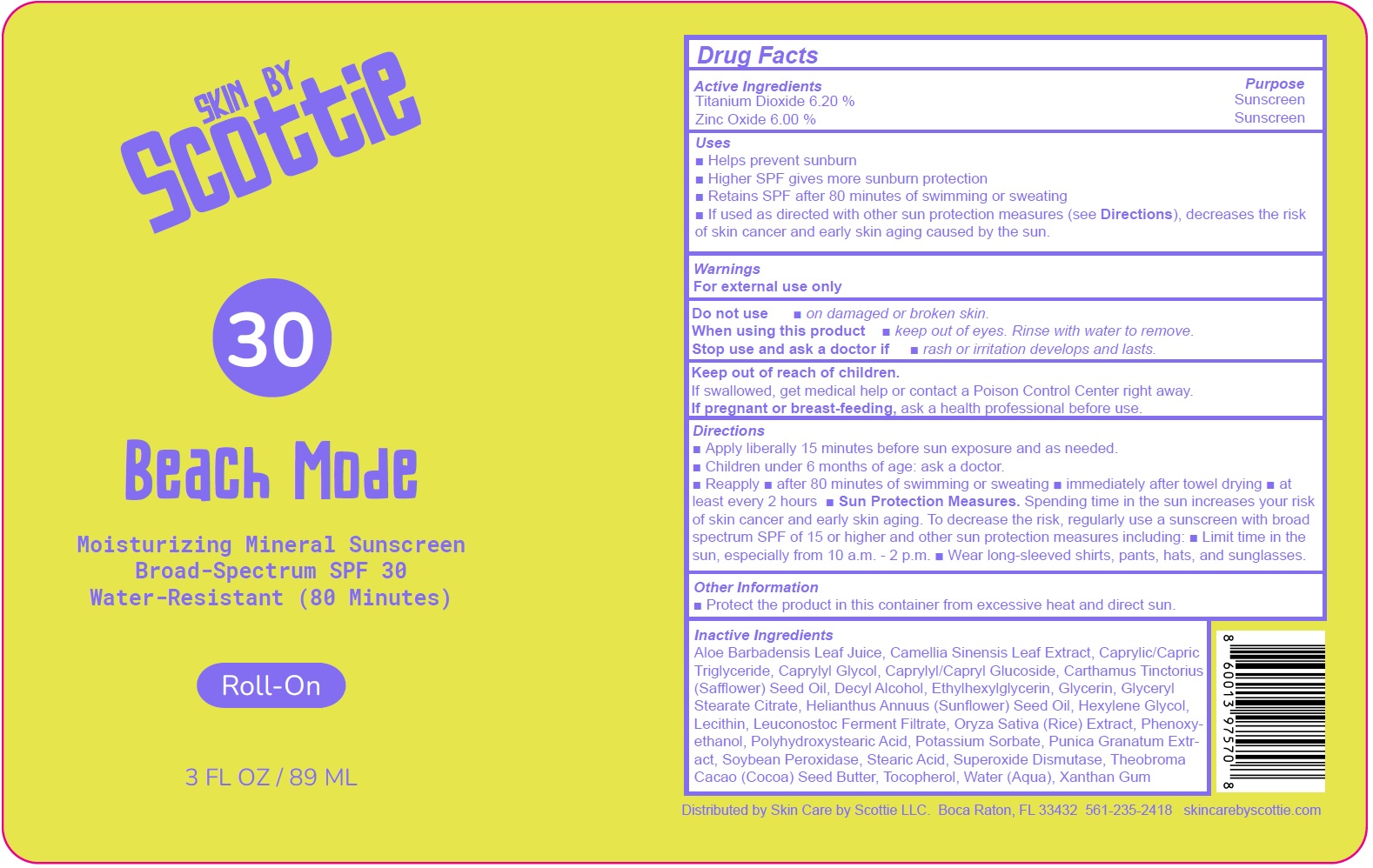 DRUG LABEL: Skin by Scottie Beach Mode Mineral Sunscreen Roll-On SPF 30
NDC: 85807-616 | Form: CREAM
Manufacturer: SKIN CARE BY SCOTTIE LLC
Category: otc | Type: HUMAN OTC DRUG LABEL
Date: 20250616

ACTIVE INGREDIENTS: TITANIUM DIOXIDE 62 mg/1 mL; ZINC OXIDE 60 mg/1 mL
INACTIVE INGREDIENTS: ALOE VERA LEAF JUICE; GREEN TEA LEAF; MEDIUM-CHAIN TRIGLYCERIDES; CAPRYLYL GLYCOL; CAPRYLYL/CAPRYL GLUCOSIDE; SAFFLOWER OIL; DECYL ALCOHOL; ETHYLHEXYLGLYCERIN; GLYCERIN; GLYCERYL STEARATE CITRATE; SUNFLOWER OIL; HEXYLENE GLYCOL; RICE GERM; PHENOXYETHANOL; POTASSIUM SORBATE; PUNICA GRANATUM ROOT BARK; STEARIC ACID; SUPEROXIDE DISMUTASE; COCOA BUTTER; TOCOPHEROL; WATER; XANTHAN GUM

Skin by Scottie Beach Mode Mineral Sunscreen Roll-On SPF 30

Active Ingredients

Titanium Dioxide 6.20 %
Zinc Oxide 6.00 %

Purpose

Sunscreen

Uses

- Helps prevent sunburn
- Higher SPF gives more sunburn protection
- Retains SPF after 80 minutes of swimming or sweating
- If used as directed with other sun protection measures (see Directions), decreases the risk of skin cancer and early skin aging caused by the sun.

Warnings

For external use only

Do not use

- on damaged or broken skin.

When using this product

- keep out of eyes. Rinse with water to remove.

Stop use and ask a doctor if

rash or irritation develops and lasts.

Keep out of reach of children.

If swallowed, get medical help or contact a Poison Control Center right away.

Directions

- Apply liberally 15 minutes before sun exposure and as needed.
- Children under 6 months of age: ask a doctor.
- Reapply • after 80 minutes of swimming or sweating • immediately after towel drying • at least every 2 hours
- Sun Protection Measures.Spending time in the sun increases your risk of skin cancer and early skin aging. To decrease the risk, regularly use a sunscreen with broad spectrum SPF of 15 or higher and other sun protection measures including:
- Limit time in the sun, especially from 10 a.m. - 2 p.m.
- Wear long-sleeved shirts, pants, hats, and sunglasses.

Other Information

- Protect the product in this container from excessive heat and direct sun.

Inactive Ingredients

Aloe Barbadensis Leaf Juice, Camellia Sinensis Leaf Extract, Caprylic/Capric Triglyceride, Caprylyl Glycol, Caprylyl/Capryl Glucoside, Carthamus Tinctorius (Safflower) Seed Oil, Decyl Alcohol, Ethylhexylglycerin, Glycerin, Glyceryl Stearate Citrate, Helianthus Annuus (Sunflower) Seed Oil, Hexylene Glycol, Lecithin, Leuconostoc Ferment Filtrate, Oryza Sativa (Rice) Extract, Phenoxyethanol, Polyhydroxystearic Acid, Potassium Sorbate, Punica Granatum Extract, Soybean Peroxidase, Stearic Acid, Superoxide Dismutase, Theobroma Cacao (Cocoa) Seed Butter, Tocopherol, Water (Aqua), Xanthan Gum